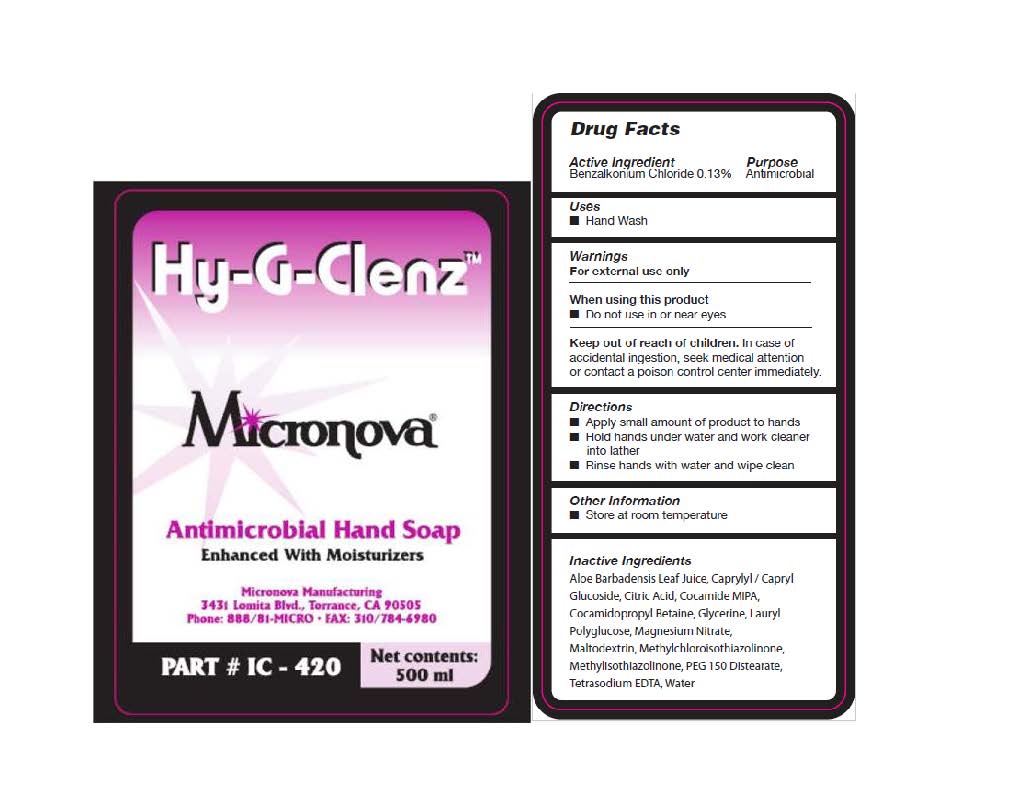 DRUG LABEL: Hy-G-Clenz
NDC: 59764-004 | Form: LIQUID
Manufacturer: Micronova Manufacturing, Inc.
Category: otc | Type: HUMAN OTC DRUG LABEL
Date: 20251106

ACTIVE INGREDIENTS: BENZALKONIUM CHLORIDE 13 kg/100 kg
INACTIVE INGREDIENTS: ALOE VERA FLOWER; CAPRYLYL/CAPRYL OLIGOGLUCOSIDE; ANHYDROUS CITRIC ACID; COCO MONOISOPROPANOLAMIDE; COCAMIDOPROPYL BETAINE; GLYCERIN; LAURYL GLUCOSIDE; MAGNESIUM NITRATE; MALTODEXTRIN; METHYLCHLOROISOTHIAZOLINONE; METHYLISOTHIAZOLINONE; PEG-150 DISTEARATE; EDETATE SODIUM; WATER

Hy-G-Clenz

ACTIVE INGREDIENT

Benzalkonium Chloride .13%

Purpose

Antimicrobial

Uses

Hand Wash

Warnings

For external use only.

When Using this Product

Do not use in or near eyes.

Keep out of reach of children.

In case of accidental ingestion, seek medical attention or contact a

Poison Control Center immediately.

Directions

- Apply small amount of product to hands.

- Hold hands under water and work cleaner into lather.

- Rinse hands with water and wipe clean.

INERT INGREDIENTS:

Aloe Barbadensis Leaf Juice, Caprylyl/Capryl Gluciside, Citric Acid, Cocamide MIPA, Cocamidopropyl Betaine, Glycerin, Lauryl Polyglucose, Magnesium Nitrate, Maltodextrin, Methylchloroisothiazolinone, Methylthiazolinone, PEG
150 Distearate, Tetrasodium EDTA, Water